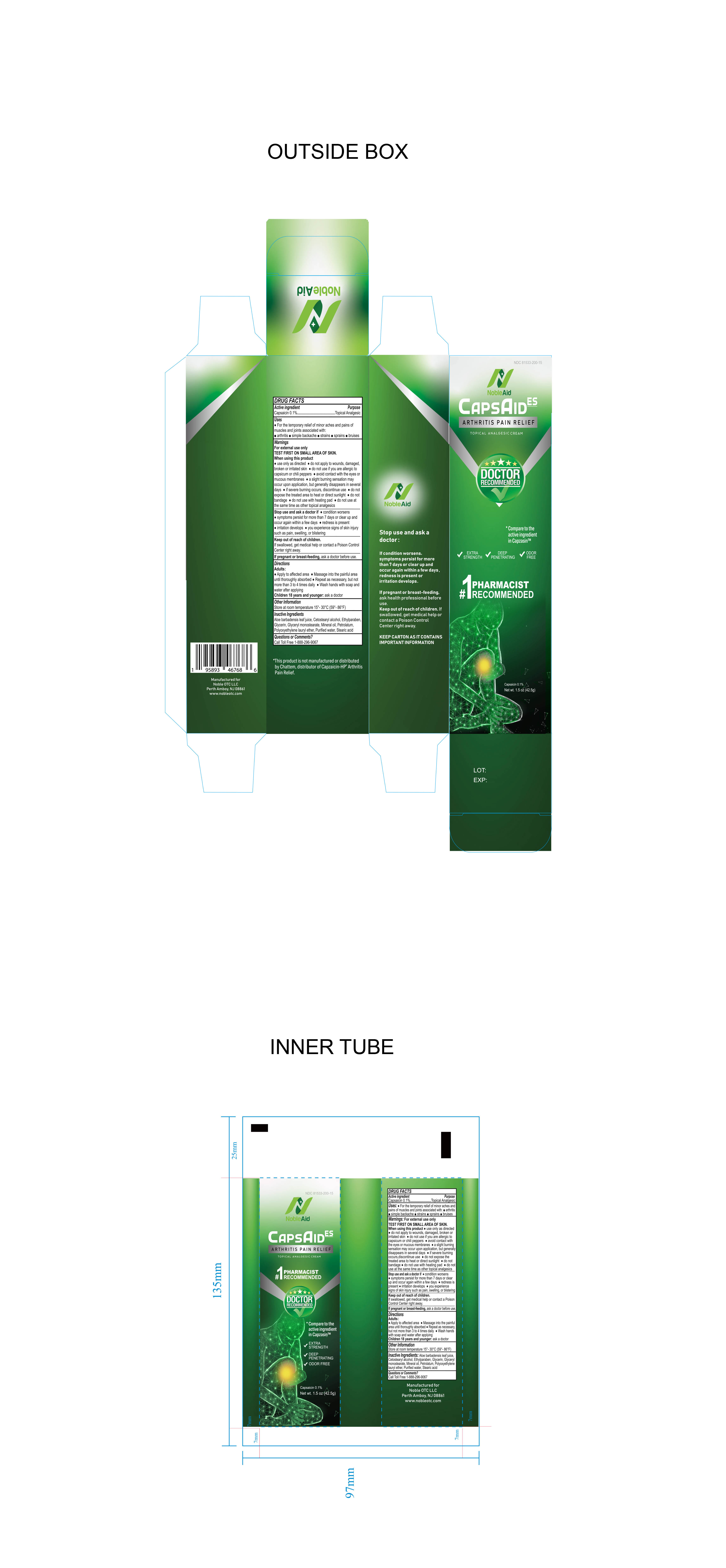 DRUG LABEL: Capsaicin Cream
NDC: 81533-200 | Form: CREAM
Manufacturer: Noble OTC LLC
Category: otc | Type: HUMAN OTC DRUG LABEL
Date: 20241218

ACTIVE INGREDIENTS: CAPSAICIN 0.1 g/100 g
INACTIVE INGREDIENTS: LAURETH-23; STEARIC ACID; CETOSTEARYL ALCOHOL; ALOE VERA LEAF; ETHYLPARABEN; MINERAL OIL; WATER; GLYCERIN; GLYCERYL MONOSTEARATE; PETROLATUM

NobleAid CapsAid ES

Active Ingredient

Capsaicin 0.1%

Purpose

Topical Analgesic

Warnings

For external use only: TEST FIRST ON SMALL AREA OF SKIN.

When using this product:

- Use only as directed
- Do not apply to wounds, damaged, broken or irritated skin
- Do not use if you are allergic to capsicum or chili peppers
- Avoid contact with the eyes or mucous membranes
- A slight burning sensation may occur upon application, but generally disappears after several days
- If severe burning occurs, discontinue use
- Do not expose the treated area to heat or direct sunlight
- Do not bandage
- Do not use with heating pad
- Do not use at the same time as other topical analgesics

Stop Use and Ask Doctor if:

- Condition worsens
- Symptoms persist for more than 7 days or clear up and occur again within a few days
- Redness is present
- irritation develops
- You experience signs of skin injury such as pain, swelling or blistering.

Keep Out of the Reach of Children

If swallowed, get medical help or contact a Poison Control Center right away.

Uses

For the temporary relief of minor aches and pains of muscles and joints associated with:

- Arthritis
- Simple Backache
- Strains
- Sprains
- Bruises

If Pregnant or Breast Feeding

Ask a doctor before use

Directions

Adults and Children over 18 years:

- Apply to affected area
- Massage into the painful area until thoroughly absorbed
- Repeat as necessary but not more than 3 to 4 times daily
- WASH HANDS WITH SOAP AND WATER AFTER APPLYING

Children 18 years and younger:

Ask a doctor

Inactive Ingredients

Aloe barbadensis leaf juice, Cetostearyl alcohol, Ethylparaben, Glycerin, Glyceryl monostearate, Mineral Oil, Petrolatum, Purified Water, Polyoxyethylene Lauryl Ether, Stearic Acid

Other Information

Store at room temperature 15°-30°F (59°-86°F)

This product is not manufactured or distributed by Chattem, distributor of Capzaicin-HP arthritis pain relief.

Questions

Questions or Comments

Please call Toll Free 1-888-296-9067

Other Information

Manufactured for

Noble OTC LLC

Perth Amboy, NJ 08861

www.nobleotc.com

This product is not manufactured or distributed by Chattem, a distributor of Capzaicin-HP Arthritis Pain Relief